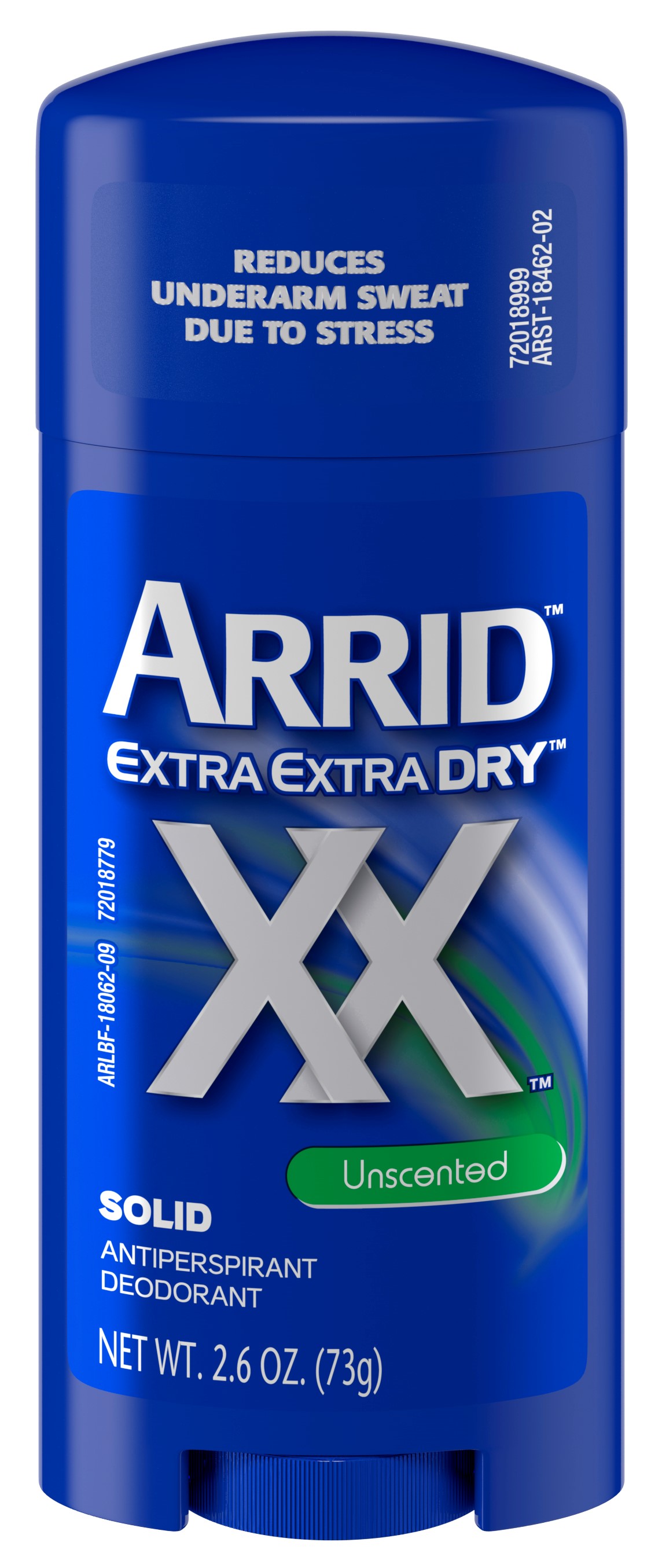 DRUG LABEL: Arrid Extra Extra Dry Unscented Solid
NDC: 10237-866 | Form: STICK
Manufacturer: Church & Dwight Co., Inc.
Category: otc | Type: HUMAN OTC DRUG LABEL
Date: 20241120

ACTIVE INGREDIENTS: ALUMINUM CHLOROHYDRATE 0.19 g/1 g
INACTIVE INGREDIENTS: TALC; PETROLATUM; ETHYLENE BRASSYLATE; PPG-14 BUTYL ETHER; CYCLOMETHICONE 5; STEARYL ALCOHOL; C12-20 ALKYL BENZOATE; HYDROGENATED CASTOR OIL

Arrid Extra Extra Dry Unscented Solid

ACTIVE INGREDIENT

Aluminum Chlorohydrate 19%

PURPOSE

Antiperspirant

INDICATIONS AND USAGE

Usereduces underarm perspiration

WARNINGS

For external use only

Do not use on broken skin

Stop use ifrash or irritation occurs

Ask a doctor before use if you havekidney disease

Keep out of reach of children.If swallowed, get medical help or contact a Poison Control Center right away.

Directions

Apply a thin layer to underarms only

INACTIVE INGREDIENT

PPG-14 Butyl Ether, Cyclopentasiloxane, Stearyl Alcohol, C12-15 Alkyl Benzoate, Talc, Hydrogenated Castor Oil, Petrolatum, Ethylene Brassylate

QUESTIONS

? 1-800-248-8820

M-F 9-5 ET

Manufactured by

Church & Dwight Co.,

Inc. Ewing, NJ 08628

www.arrid.com

PACKAGE LABEL

REDUCES

UNDERARM SWEAT

DUE TO STRESS

ARRID

EXTRA EXTRA Dry

XX

Unscented

SOLID

ANTIPERSPIRANT

DEODORANT

NET WT. 2.6 OZ. (73g)